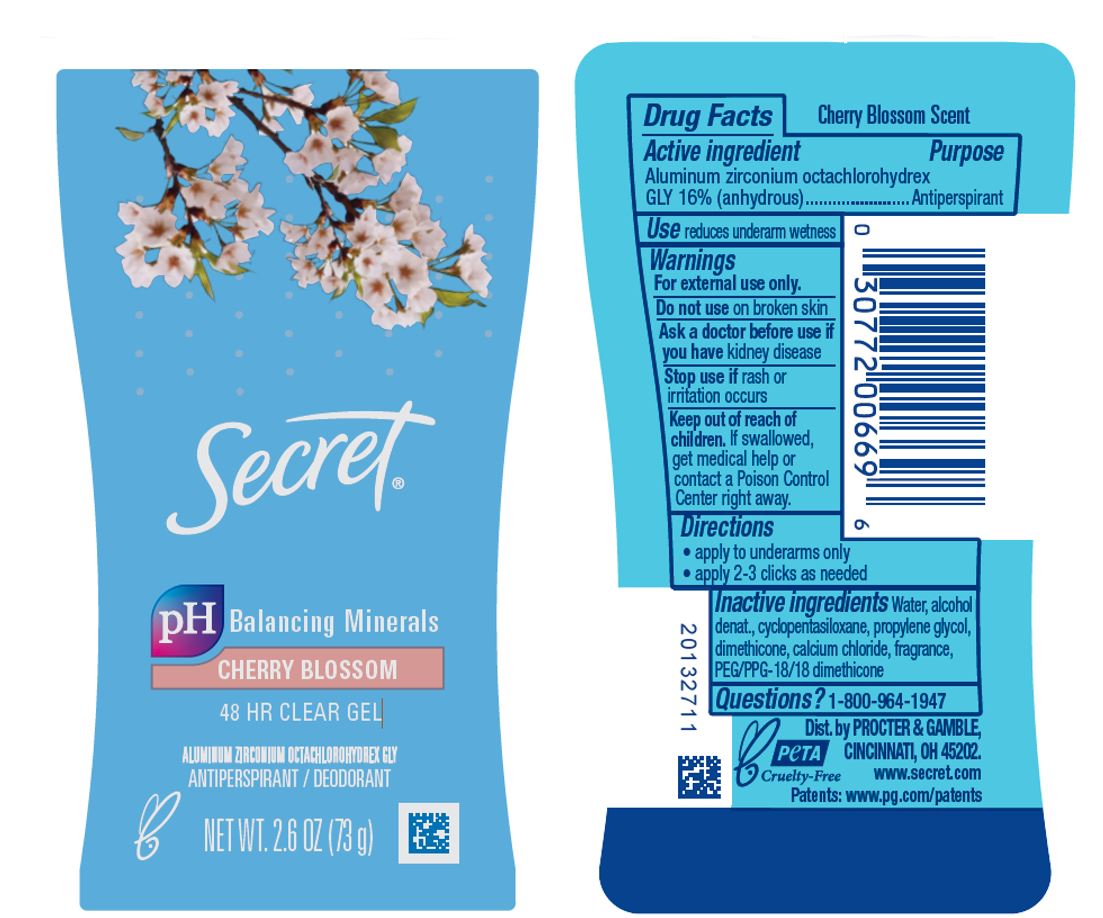 DRUG LABEL: Secret Cherry Blossom Clear
NDC: 69423-655 | Form: GEL
Manufacturer: The Procter & Gamble Manufacturing Company
Category: otc | Type: HUMAN OTC DRUG LABEL
Date: 20260106

ACTIVE INGREDIENTS: ALUMINUM ZIRCONIUM OCTACHLOROHYDREX GLY 16 g/100 g
INACTIVE INGREDIENTS: WATER; ALCOHOL; CYCLOMETHICONE 5; PROPYLENE GLYCOL; DIMETHICONE; CALCIUM CHLORIDE; PEG/PPG-18/18 DIMETHICONE

Secret® Cherry Blossom Clear

Drug Facts

Active ingredient

Aluminum zirconium octachlorohydrex Gly 16% (anhydrous)

Purpose

Antiperspirant

Use

- reduces underarm wetness

Warnings

For external use only.

Do not use on broken skin

Ask a doctor before use if you have kidney disease

Stop use if rash or irritation occurs

Keep out of reach of children. If swallowed, get medical help or contact a Poison Control Center right away.

Directions

- apply to underarms only
- apply 2-3 clicks as needed

Inactive ingredients

water, alcohol denat., cyclopentasiloxane, propylene glycol, dimethicone, calcium chloride, fragrance, PEG/PPG-18/18 dimethicone

Questions?

1-800-964-1947

Dist. by PROCTER & GAMBLE,
CINCINNATI, OH 45202.

PRINCIPAL DISPLAY PANEL - 73 g Cylinder Label

Secret®

pH Balancing Minerals

Cherry Blossom

48HR CLEAR GEL

ALUMINUM ZIRCONIUM OCTACHLOROHYDREX GLY
ANTIPERSPIRANT / DEODORANT

NET WT. 2.6 OZ (73 g)